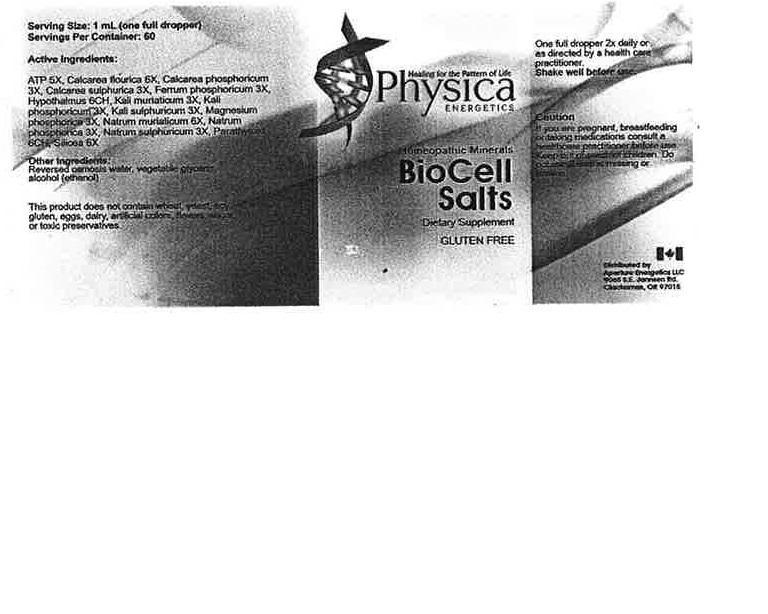 DRUG LABEL: BioCell Salts
NDC: 54118-7134 | Form: SOLUTION/ DROPS
Manufacturer: ABCO Laboratories, Inc.
Category: homeopathic | Type: HUMAN OTC DRUG LABEL
Date: 20150714

ACTIVE INGREDIENTS: CALCIUM FLUORIDE 6 [hp_X]/60 mL; CALCIUM SULFATE 3 [hp_X]/60 mL; POTASSIUM CHLORIDE 3 [hp_X]/60 mL; CALCIUM PHOSPHATE 3 [hp_X]/60 mL; FERRUM PHOSPHORICUM 3 [hp_X]/60 mL; POTASSIUM SULFATE 3 [hp_X]/60 mL; SODIUM CHLORIDE 6 [hp_X]/60 mL; SODIUM SULFATE 3 [hp_X]/60 mL; MAGNESIUM PHOSPHATE ANHYDROUS 3 [hp_X]/60 mL; SODIUM PHOSPHATE 3 [hp_X]/60 mL; SILICON DIOXIDE 6 [hp_X]/60 mL; ADENOSINE TRIPHOSPHATE 5 [hp_X]/60 mL; BOS TAURUS PARATHYROID GLAND 6 [hp_C]/60 mL; BOS TAURUS HYPOTHALAMUS 6 [hp_C]/60 mL
INACTIVE INGREDIENTS: WATER; ALCOHOL; GLYCERIN

BioCell Salt

WARNINGS

- If you are pregnant, breastfeeding or taking medications consult a healthcare practitioner before use.
- Keep out of reach of children.
- Do not use if seal is missing or broken.

INACTIVE INGREDIENT

WATER:REVERSE OSMOSI, ETHYL ALCOHOL:GRAIN:190 PROOF, GLYCERINE.

ACTIVE INGREDIENT

Calcarea Flourica 6x, Calcarea Sulphurica 3x, Kali Muriaticum 3x, Calcarea Phosphoricum 3x, Ferrum Phosphoricum 3x, Kali Sulphuricum 3x, Natrum Muriaticum 6x, Natrum Sulphuricum 3x, Magnesium Phosphorica 3x, Natrum Phosphorica 3x, Silicea 6x, AATP 5x, Parathyroid 6c, Hypothalamus 6c.

KEEP OUT OF REACH OF CHILDREN!

DOSAGE AND ADMINISTRATION

- One full dropper 2x daily or as directed by a healthcare practitioner.
- Shake well before use.

PURPOSE

Homeopathic Minerals

INDICATIONS AND USAGE

Dietary Suppliment.